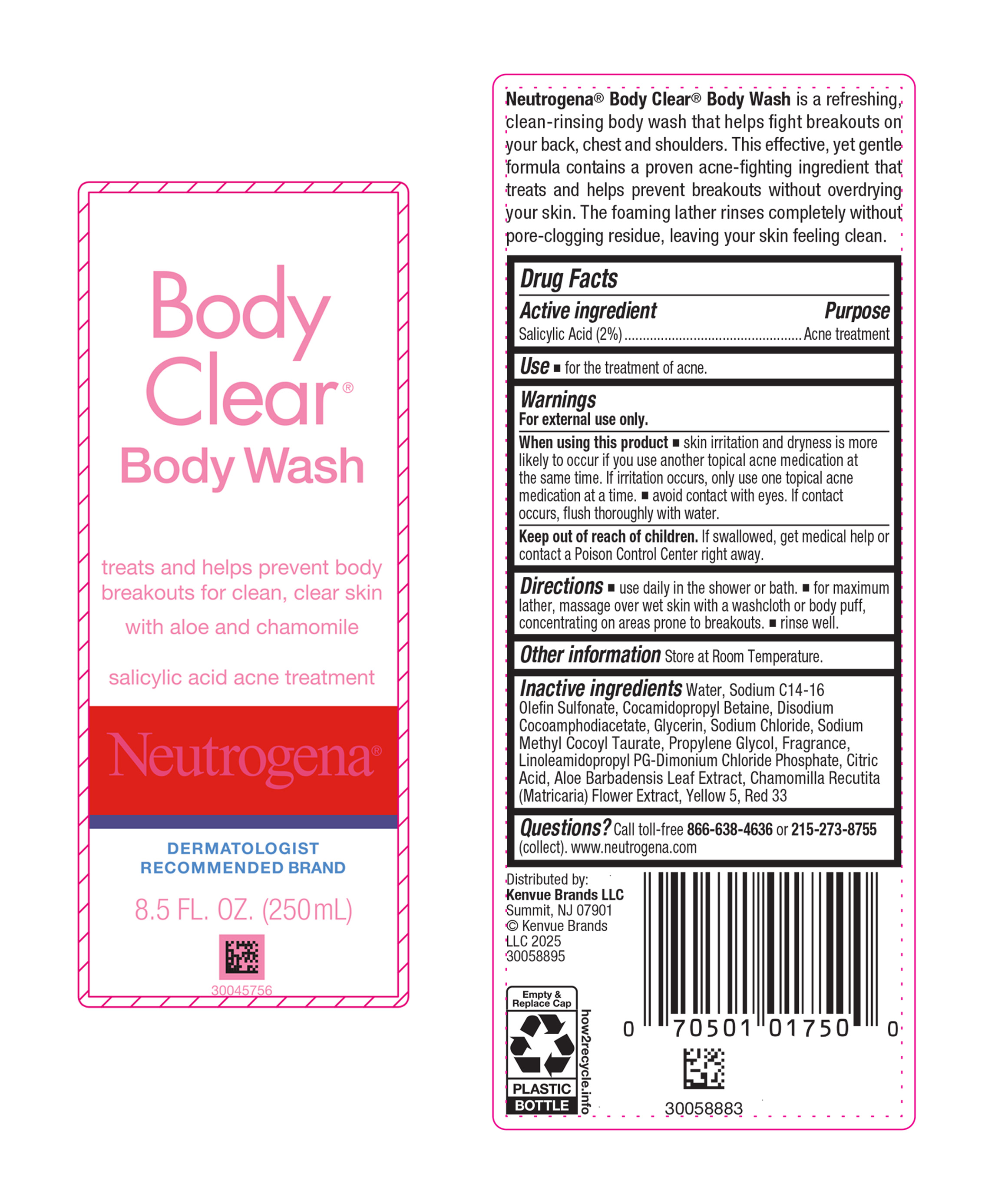 DRUG LABEL: Neutrogena Body Clear Body Wash
NDC: 69968-0655 | Form: LIQUID
Manufacturer: Kenvue Brands LLC
Category: otc | Type: HUMAN OTC DRUG LABEL
Date: 20250418

ACTIVE INGREDIENTS: SALICYLIC ACID 20 mg/1 mL
INACTIVE INGREDIENTS: WATER; SODIUM C14-16 OLEFIN SULFONATE; COCAMIDOPROPYL BETAINE; DISODIUM COCOAMPHODIACETATE; GLYCERIN; SODIUM CHLORIDE; SODIUM METHYL COCOYL TAURATE; PROPYLENE GLYCOL; LINOLEAMIDOPROPYL PROPYLENE GLYCOL-DIMONIUM CHLORIDE PHOSPHATE; CITRIC ACID MONOHYDRATE; ALOE VERA LEAF; CHAMOMILE; FD&C YELLOW NO. 5; D&C RED NO. 33

Neutrogena® Body Clear® Body Wash

Drug Facts

Active ingredient

Salicylic Acid 2%

Purpose

Acne Treatment

Use

- for the treatment of acne.

Warnings

For external use only.

When using this product

- skin irritation and dryness is more likely to occur if you use another topical acne medication at the same time. If irritation occurs, only use one topical acne medication at a time.
- avoid contact with eyes. If contact occurs, flush thoroughly with water.

Keep out of reach of children. If swallowed, get medical help or contact a Poison Control Center right away.

Directions

- use daily in the shower or bath.
- for maximum lather, massage over wet skin with a washcloth or body puff, concentrating on areas prone to breakouts.
- rinse well.

Other information

Store at Room Temperature.

Inactive ingredients

Water, Sodium C14-16 Olefin Sulfonate, Cocamidopropyl Betaine, Disodium Cocoamphodiacetate, Glycerin, Sodium Chloride, Sodium Methyl Cocoyl Taurate, Propylene Glycol, Fragrance, Linoleamidopropyl PG-Dimonium Chloride Phosphate, Citric Acid, Aloe Barbadensis Leaf Extract, Chamomilla Recutita (Matricaria) Flower Extract, Yellow 5, Red 33

Questions?

Call toll-free 866-638-4636 or 215-273-8755 (collect). www.neutrogena.com

Distributed by:
Kenvue Brands LLC
Summit, NJ 07901

PRINCIPAL DISPLAY PANEL - 250 mL Bottle Label

Body
Clear®
Body Wash

treats and helps prevent body
breakouts for clean, clear skin

with aloe and chamomile

salicylic acid acne treatment

Neutrogena ®

DERMATOLOGIST
RECOMMENDED BRAND

8.5 FL. OZ. (250mL)